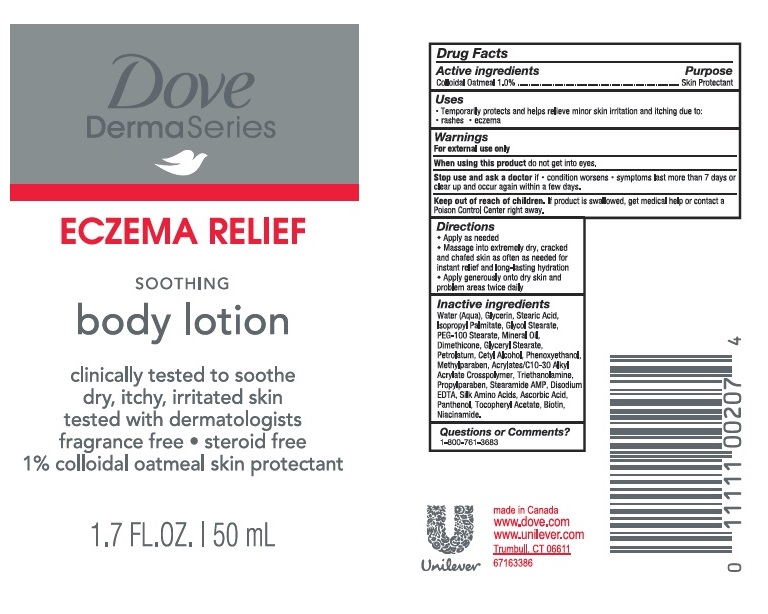 DRUG LABEL: Dove
NDC: 64942-1870 | Form: LOTION
Manufacturer: Conopco, Inc. d/b/a/ Unilever
Category: otc | Type: HUMAN OTC DRUG LABEL
Date: 20241107

ACTIVE INGREDIENTS: OATMEAL 1 g/100 mL
INACTIVE INGREDIENTS: WATER; GLYCERIN; STEARIC ACID; ISOPROPYL PALMITATE; GLYCOL STEARATE; DIMETHICONE; GLYCERYL MONOSTEARATE; PETROLATUM; CETYL ALCOHOL; PHENOXYETHANOL; METHYLPARABEN; CARBOMER INTERPOLYMER TYPE A (ALLYL SUCROSE CROSSLINKED); TROLAMINE; PROPYLPARABEN; STEARAMIDE AMP; EDETATE DISODIUM; PEG-100 STEARATE; MINERAL OIL; AMINO ACIDS, SILK; ASCORBIC ACID; .ALPHA.-TOCOPHEROL ACETATE; PANTHENOL; NIACINAMIDE; BIOTIN

Dove DermaSeries Eczema Relief Soothing Body Lotion

Description

DOVE DERMASERIES ECZEMA RELIEF SOOTHING BODY LOTION - (colloidal oatmeal) lotion

Drug Facts

Active ingredient
Colloidal Oatmeal (1%)

Purpose

Skin Protectant

Uses

temporarily protects and helps relieve minor skin irritation and itching due to:

- rashes
- eczema

Warnings

For external use only
When using this product do not get into eyes.r.
Stop use and ask a doctor if

- condition worsens
- symptoms last more than 7 days or clear up and occur again within a few days

Keep out of reach of children. If product is swallowed, get medical help or contact a Poison Control Center right away.

Directions

Apply as needed
Massage into extremely dry, cracked and chafed skin as often as needed for instant relief andlong-lasting hydration
Apply generously onto dry skin and problem areas twice daily

Inactive ingredients

Water (Aqua), Glycerin, Stearic Acid, Isopropyl Palmitate, Glycol Stearate, PEG-100 Stearate, Mineral Oil, Dimethicone, Glyceryl Stearate, Petrolatum, Cetyl Alcohol, Phenoxyethanol, Methylparaben, Acrylates/C10-30 Alkyl Acrylate Crosspolymer, Triethanolamine, Propylparaben, Stearamide AMP, Disodium EDTA, Silk Amino Acids, Ascorbic Acid, Panthenol, Tocopheryl Acetate, Biotin, Niacinamide.

Questions or comments?

1-800-761-3683